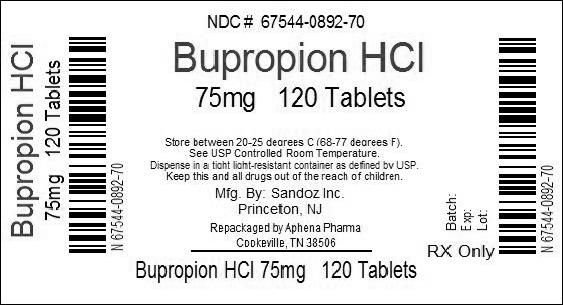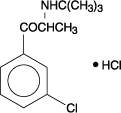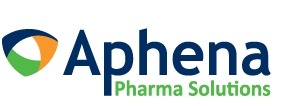 DRUG LABEL: Bupropion Hydrochloride
NDC: 67544-892 | Form: TABLET, FILM COATED
Manufacturer: Aphena Pharma Solutions - Tennessee, LLC
Category: prescription | Type: HUMAN PRESCRIPTION DRUG LABEL
Date: 20140521

ACTIVE INGREDIENTS: BUPROPION HYDROCHLORIDE 75 mg/1 1
INACTIVE INGREDIENTS: CELLULOSE, MICROCRYSTALLINE; FD&C BLUE NO. 2; FD&C RED NO. 40; HYPROMELLOSE 2910 (15 MPA.S); POTASSIUM CHLORIDE; STARCH, CORN; STEARIC ACID; TITANIUM DIOXIDE; TRIETHYL CITRATE

BuPROPion Hydrochloride Tablets, USP

WARNING

Suicidality and Antidepressant Drugs

Use in Treating Psychiatric Disorders: Antidepressants increased the risk compared to placebo of suicidal thinking and behavior (suicidality) in children, adolescents, and young adults in short-term studies of major depressive disorder (MDD) and other psychiatric disorders. Anyone considering the use of bupropion hydrochloride tablets or any other antidepressant in a child, adolescent, or young adult must balance this risk with the clinical need. Short-term studies did not show an increase in the risk of suicidality with antidepressants compared to placebo in adults beyond age 24; there was a reduction in risk with antidepressants compared to placebo in adults aged 65 and older. Depression and certain other psychiatric disorders are themselves associated with increases in the risk of suicide. Patients of all ages who are started on antidepressant therapy should be monitored appropriately and observed closely for clinical worsening, suicidality, or unusual changes in behavior. Families and caregivers should be advised of the need for close observation and communication with the prescriber. Bupropion hydrochloride tablets are not approved for use in pediatric patients. (See WARNINGS: Clinical Worsening and Suicide Risk in Treating Psychiatric Disorders, PRECAUTIONS: Information for Patients, and PRECAUTIONS: Pediatric Use.)

Use in Smoking Cessation Treatment: Bupropion hydrochloride, bupropion hydrochloride, the sustained-release formulation, and bupropion hydrochloride, the extended-release formulation, are not approved for smoking cessation treatment, but bupropion under the name ZYBAN® (bupropion hydrochloride) Sustained-Release Tablets is approved for this use. Serious neuropsychiatric events, including but not limited to depression, suicidal ideation, suicide attempt, and completed suicide have been reported in patients taking bupropion for smoking cessation. Some cases may have been complicated by the symptoms of nicotine withdrawal in patients who stopped smoking. Depressed mood may be a symptom of nicotine withdrawal. Depression, rarely including suicidal ideation, has been reported in smokers undergoing a smoking cessation attempt without medication. However, some of these symptoms have occurred in patients taking bupropion who continued to smoke.

All patients being treated with bupropion for smoking cessation treatment should be observed for neuropsychiatric symptoms including changes in behavior, hostility, agitation, depressed mood, and suicide-related events, including ideation, behavior, and attempted suicide. These symptoms, as well as worsening of pre-existing psychiatric illness and completed suicide have been reported in some patients attempting to quit smoking while taking ZYBAN in the postmarketing experience. When symptoms were reported, most were during treatment with ZYBAN, but some were following discontinuation of treatment with ZYBAN. These events have occurred in patients with and without pre-existing psychiatric disease; some have experienced worsening of their psychiatric illnesses. Patients with serious psychiatric illness such as schizophrenia, bipolar disorder, and major depressive disorder did not participate in the premarketing studies of ZYBAN.

Advise patients and caregivers that the patient using bupropion for smoking cessation should stop taking bupropion and contact a healthcare provider immediately if agitation, hostility, depressed mood, or changes in thinking or behavior that are not typical for the patient are observed, or if the patient develops suicidal ideation or suicidal behavior. In many postmarketing cases, resolution of symptoms after discontinuation of ZYBAN was reported, although in some cases the symptoms persisted; therefore, ongoing monitoring and supportive care should be provided until symptoms resolve.

The risks of using bupropion for smoking cessation should be weighed against the benefits of its use. bupropion hydrochloride tablets has been demonstrated to increase the likelihood of abstinence from smoking for as long as 6 months compared to treatment with placebo. The health benefits of quitting smoking are immediate and substantial. (See WARNINGS: Neuropsychiatric Symptoms and Suicide Risk in Smoking Cessation Treatment and PRECAUTIONS: Information for Patients.)

DESCRIPTION

Bupropion hydrochloride, an antidepressant of the aminoketone class, is chemically unrelated to tricyclic, tetracyclic, selective serotonin re-uptake inhibitor, or other known antidepressant agents. Its structure closely resembles that of diethylpropion; it is related to phenylethylamines. It is designated as (±)-1-(3-chlorophenyl)-2-[(1,1-dimethylethyl)amino]-1-propanone hydrochloride. The molecular weight is 276.2. The molecular formula is C13H18CINO•HCI. Bupropion hydrochloride powder is white, crystalline, and highly soluble in water. It has a bitter taste and produces the sensation of local anesthesia on the oral mucosa. It has the following structural formula:

Each bupropion hydrochloride tablet intended for oral administration contains 75 mg or 100 mg bupropion hydrochloride. In addition, each bupropion hydrochloride tablet contains the following inactive ingredients: FD&C Blue No. 2 aluminum lake, FD&C Red No. 40 aluminum lake, hydroxypropyl methylcellulose, microcrystalline cellulose, potassium chloride, pregelatinized starch, stearic acid, titanium dioxide, and triethyl citrate.

CLINICAL PHARMACOLOGY

Pharmacodynamics

The neurochemical mechanism of the antidepressant effect of bupropion is not known. Bupropion is a relatively weak inhibitor of the neuronal uptake of norepinephrine and dopamine, and does not inhibit monoamine oxidase or the re-uptake of serotonin.

Bupropion produces dose-related central nervous system (CNS) stimulant effects in animals, as evidenced by increased locomotor activity, increased rates of responding in various schedule-controlled operant behavior tasks, and, at high doses, induction of mild stereotyped behavior.

Bupropion causes convulsions in rodents and dogs at doses approximately tenfold the dose recommended as the human antidepressant dose.

Pharmacokinetics

Bupropion is a racemic mixture. The pharmacological activity and pharmacokinetics of the individual enantiomers have not been studied. In humans, following oral administration of bupropion hydrochloride tablets, peak plasma bupropion concentrations are usually achieved within 2 hours, followed by a biphasic decline. The terminal phase has a mean half-life of 14 hours, with a range of 8 to 24 hours. The distribution phase has a mean half-life of 3 to 4 hours. The mean elimination half-life (±SD) of bupropion after chronic dosing is 21 (±9) hours, and steady-state plasma concentrations of bupropion are reached within 8 days. Plasma bupropion concentrations are dose-proportional following single doses of 100 to 250 mg; however, it is not known if the proportionality between dose and plasma level is maintained in chronic use.

Absorption

The absolute bioavailability of bupropion hydrochloride tablets in humans has not been determined because an intravenous formulation for human use is not available. However, it appears likely that only a small proportion of any orally administered dose reaches the systemic circulation intact.

Distribution

In vitro tests show that bupropion is 84% bound to human plasma protein at concentrations up to 200 mcg/mL. The extent of protein binding of the hydroxybupropion metabolite is similar to that for bupropion, whereas the extent of protein binding of the threohydrobupropion metabolite is about half that seen with bupropion.

Metabolism

Bupropion is extensively metabolized in humans. Three metabolites have been shown to be active: hydroxybupropion, which is formed via hydroxylation of the tert-butyl group of bupropion, and the amino-alcohol isomers threohydrobupropion and erythrohydrobupropion, which are formed via reduction of the carbonyl group. In vitro findings suggest that cytochrome P450IIB6 (CYP2B6) is the principal isoenzyme involved in the formation of hydroxybupropion, while cytochrome P450 isoenzymes are not involved in the formation of threohydrobupropion. Oxidation of the bupropion side chain results in the formation of a glycine conjugate of metachlorobenzoic acid, which is then excreted as the major urinary metabolite. The potency and toxicity of the metabolites relative to bupropion have not been fully characterized. However, it has been demonstrated in an antidepressant screening test in mice that hydroxybupropion is one-half as potent as bupropion, while threohydrobupropion and erythrohydrobupropion are 5-fold less potent than bupropion. This may be of clinical importance because their plasma concentrations are as high or higher than those of bupropion.

Because bupropion is extensively metabolized, there is the potential for drug-drug interactions, particularly with those agents that are metabolized by or which inhibit/induce the cytochrome P450IIB6 (CYP2B6) isoenzyme, such as ritonavir or efavirenz. In a healthy volunteer study, ritonavir at a dose of 100 mg twice daily reduced the AUC and Cmax of bupropion by 22% and 21%, respectively. The exposure of the hydroxybupropion metabolite was decreased by 23%, the threohydrobupropion decreased by 38%, and the erythrohydrobupropion decreased by 48%.

In a second healthy volunteer study, ritonavir at a dose of 600 mg twice daily decreased the AUC and the Cmax of bupropion by 66% and 62%, respectively. The exposure of the hydroxybupropion metabolite was decreased by 78%, the threohydrobupropion decreased by 50%, and the erythrohydrobupropion decreased by 68%.

In another healthy volunteer study, KALETRA® (lopinavir 400 mg/ritonavir 100 mg twice daily) decreased bupropion AUC and Cmax by 57%. The AUC and Cmax of hydroxybupropion were decreased by 50% and 31%, respectively (see PRECAUTIONS: Drug Interactions).

In a study in healthy volunteers, efavirenz 600 mg once daily for 2 weeks reduced the AUC and Cmax of bupropion by approximately 55% and 34%, respectively. The AUC of hydroxybupropion was unchanged, whereas Cmax of hydroxybupropion was increased by 50%.

Although bupropion is not metabolized by cytochrome P450IID6 (CYP2D6), there is the potential for drug-drug interactions when bupropion is coadministered with drugs metabolized by this isoenzyme (see PRECAUTIONS: Drug Interactions).

Following a single dose in humans, peak plasma concentrations of hydroxybupropion occur approximately 3 hours after administration of bupropion hydrochloride tablets. Peak plasma concentrations of hydroxybupropion are approximately 10 times the peak level of the parent drug at steady state. The elimination half-life of hydroxybupropion is approximately 20 (±5) hours, and its AUC at steady state is about 17 times that of bupropion. The times to peak concentrations for the erythrohydrobupropion and threohydrobupropion metabolites are similar to that of the hydroxybupropion metabolite. However, their elimination half-lives are longer, 33 (±10) and 37 (±13) hours, respectively, and steady-state AUCs are 1.5 and 7 times that of bupropion, respectively.

Bupropion and its metabolites exhibit linear kinetics following chronic administration of 300 to 450 mg/day.

Elimination

Following oral administration of 200 mg of ^14C-bupropion in humans, 87% and 10% of the radioactive dose were recovered in the urine and feces, respectively. However, the fraction of the oral dose of bupropion hydrochloride tablets excreted unchanged was only 0.5%, a finding consistent with the extensive metabolism of bupropion.

Populations Subgroups

Factors or conditions altering metabolic capacity (e.g., liver disease, congestive heart failure [CHF], age, concomitant medications, etc.) or elimination may be expected to influence the degree and extent of accumulation of the active metabolites of bupropion. The elimination of the major metabolites of bupropion may be affected by reduced renal or hepatic function because they are moderately polar compounds and are likely to undergo further metabolism or conjugation in the liver prior to urinary excretion.

Hepatic

The effect of hepatic impairment on the pharmacokinetics of bupropion was characterized in 2 single-dose studies, one in patients with alcoholic liver disease and one in patients with mild-to-severe cirrhosis. The first study showed that the half-life of hydroxybupropion was significantly longer in 8 patients with alcoholic liver disease than in 8 healthy volunteers (32 ± 14 hours versus 21 ± 5 hours, respectively). Although not statistically significant, the AUCs for bupropion and hydroxybupropion were more variable and tended to be greater (by 53% to 57%) in volunteers with alcoholic liver disease. The differences in half-life for bupropion and the other metabolites in the 2 patient groups were minimal.

The second study showed that there were no statistically significant differences in the pharmacokinetics of bupropion and its active metabolites in 9 patients with mild-to-moderate hepatic cirrhosis compared to 8 healthy volunteers. However, more variability was observed in some of the pharmacokinetic parameters for bupropion (AUC, Cmax, and Tmax) and its active metabolites (t1/2) in patients with mild-to-moderate hepatic cirrhosis. In addition, in patients with severe hepatic cirrhosis, the bupropion Cmax and AUC were substantially increased (mean difference: by approximately 70% and 3-fold, respectively) and more variable when compared to values in healthy volunteers; the mean bupropion half-life was also longer (29 hours in patients with severe hepatic cirrhosis vs. 19 hours in healthy subjects). For the metabolite hydroxybupropion, the mean Cmax was approximately 69% lower. For the combined amino-alcohol isomers threohydrobupropion and erythrohydrobupropion, the mean Cmax was approximately 31% lower. The mean AUC increased by about 1^1/2-fold for hydroxybupropion and about 2^1/2-fold for threo/erythrohydrobupropion. The median Tmax was observed 19 hours later for hydroxybupropion and 31 hours later for threo/erythrohydrobupropion. The mean half-lives for hydroxybupropion and threo/erythrohydrobupropion were increased 5- and 2-fold, respectively, in patients with severe hepatic cirrhosis compared to healthy volunteers (see WARNINGS, PRECAUTIONS, and DOSAGE AND ADMINISTRATION).

Renal

There is limited information on the pharmacokinetics of bupropion in patients with renal impairment. An inter-study comparison between normal subjects and patients with end-stage renal failure demonstrated that the parent drug Cmax and AUC values were comparable in the 2 groups, whereas the hydroxybupropion and threohydrobupropion metabolites had a 2.3- and 2.8-fold increase, respectively, in AUC for patients with end-stage renal failure. A second study, comparing normal subjects and patients with moderate-to-severe renal impairment (GFR 30.9 ± 10.8 mL/min) showed that exposure to a single 150 mg dose of sustained-release bupropion was approximately 2-fold higher in patients with impaired renal function while levels of the hydroxybupropion and threo/erythrohydrobupropion (combined) metabolites were similar in the 2 groups. The elimination of bupropion and/or the major metabolites of bupropion may be reduced by impaired renal function (see PRECAUTIONS: Renal Impairment).

Left Ventricular Dysfunction

During a chronic dosing study in 14 depressed patients with left ventricular dysfunction (history of CHF or an enlarged heart on x-ray), no apparent effect on the pharmacokinetics of bupropion or its metabolites was revealed, compared to healthy volunteers.

Age

The effects of age on the pharmacokinetics of bupropion and its metabolites have not been fully characterized, but an exploration of steady-state bupropion concentrations from several depression efficacy studies involving patients dosed in a range of 300 to 750 mg/day, on a 3 times daily schedule, revealed no relationship between age (18 to 83 years) and plasma concentration of bupropion. A single-dose pharmacokinetic study demonstrated that the disposition of bupropion and its metabolites in elderly subjects was similar to that of younger subjects. These data suggest there is no prominent effect of age on bupropion concentration; however, another pharmacokinetic study, single and multiple dose, has suggested that the elderly are at increased risk for accumulation of bupropion and its metabolites (see PRECAUTIONS: Geriatric Use).

Gender

A single-dose study involving 12 healthy male and 12 healthy female volunteers revealed no sex-related differences in the pharmacokinetic parameters of bupropion.

Smokers

The effects of cigarette smoking on the pharmacokinetics of bupropion were studied in 34 healthy male and female volunteers; 17 were chronic cigarette smokers and 17 were nonsmokers. Following oral administration of a single 150 mg dose of bupropion, there were no statistically significant differences in Cmax, half-life, Tmax, AUC or clearance of bupropion or its active metabolites between smokers and nonsmokers.

INDICATIONS AND USAGE

Bupropion hydrochloride tablets are indicated for the treatment of major depressive disorder. A physician considering bupropion hydrochloride tablets for the management of a patient’s first episode of depression should be aware that the drug may cause generalized seizures in a dose-dependent manner with an approximate incidence of 0.4% (4/1,000). This incidence of seizures may exceed that of other marketed antidepressants by as much as 4-fold. This relative risk is only an approximate estimate because no direct comparative studies have been conducted (see WARNINGS).

The efficacy of bupropion hydrochloride tablets has been established in 3 placebo-controlled trials, including 2 of approximately 3 weeks’ duration in depressed inpatients and one of approximately 6 weeks’ duration in depressed outpatients. The depressive disorder of the patients studied corresponds most closely to the Major Depression category of the APA Diagnostic and Statistical Manual III.

Major Depression implies a prominent and relatively persistent depressed or dysphoric mood that usually interferes with daily functioning (nearly every day for at least 2 weeks); it should include at least 4 of the following 8 symptoms: change in appetite, change in sleep, psychomotor agitation or retardation, loss of interest in usual activities or decrease in sexual drive, increased fatigability, feelings of guilt or worthlessness, slowed thinking or impaired concentration, and suicidal ideation or attempts.

Effectiveness of bupropion hydrochloride tablets in long-term use, that is, for more than 6 weeks, has not been systematically evaluated in controlled trials. Therefore, the physician who elects to use bupropion hydrochloride tablets for extended periods should periodically reevaluate the long-term usefulness of the drug for the individual patient.

CONTRAINDICATIONS

Bupropion hydrochloride tablets are contraindicated in patients with a seizure disorder.

Bupropion hydrochloride tablets are contraindicated in patients treated with ZYBAN (bupropion hydrochloride) Sustained-Release Tablets; Wellbutrin SR (bupropion hydrochloride), the sustained-release formulation; Wellbutrin XL (bupropion hydrochloride), the extended-release formulation; or any other medications that contain bupropion because the incidence of seizure is dose dependent.

Bupropion hydrochloride tablets are contraindicated in patients with a current or prior diagnosis of bulimia or anorexia nervosa because of a higher incidence of seizures noted in such patients treated with bupropion hydrochloride tablets.

Bupropion hydrochloride tablets are contraindicated in patients undergoing abrupt discontinuation of alcohol or sedatives (including benzodiazepines).

The use of monoamine oxidase inhibitors or MAOIs (intended to treat psychiatric disorders) concomitantly with bupropion hydrochloride tablets or within 14 days of stopping treatment with bupropion hydrochloride tablets is contraindicated. There is an increased risk of hypertensive reactions when bupropion is used concomitantly with other drugs that inhibit the reuptake of dopamine or norepinephrine or inhibit their metabolism (e.g., MAOIs). The use of bupropion hydrochloride tablets within 14 days of stopping treatment with an MAOI is also contraindicated. Starting bupropion hydrochloride tablets in a patient treated with reversible MAOIs such as linezolid or intravenous methylene blue is contraindicated (see DOSAGE AND ADMINISTRATION and Drug Interactions).

Bupropion hydrochloride tablets are contraindicated in patients who have shown an allergic response to bupropion or the other ingredients that make up bupropion hydrochloride tablets.

WARNINGS

Clinical Worsening and Suicide Risk in Treating Psychiatric Disorders

Patients with major depressive disorder (MDD), both adult and pediatric, may experience worsening of their depression and/or the emergence of suicidal ideation and behavior (suicidality) or unusual changes in behavior, whether or not they are taking antidepressant medications, and this risk may persist until significant remission occurs. Suicide is a known risk of depression and certain other psychiatric disorders, and these disorders themselves are the strongest predictors of suicide. There has been a long-standing concern, however, that antidepressants may have a role in inducing worsening of depression and the emergence of suicidality in certain patients during the early phases of treatment. Pooled analyses of short-term placebo-controlled trials of antidepressant drugs (SSRIs and others) showed that these drugs increase the risk of suicidal thinking and behavior (suicidality) in children, adolescents, and young adults (ages 18-24) with major depressive disorder (MDD) and other psychiatric disorders. Short-term studies did not show an increase in the risk of suicidality with antidepressants compared to placebo in adults beyond age 24; there was a reduction with antidepressants compared to placebo in adults aged 65 and older.

The pooled analyses of placebo-controlled trials in children and adolescents with MDD, obsessive compulsive disorder (OCD), or other psychiatric disorders included a total of 24 short-term trials of 9 antidepressant drugs in over 4,400 patients. The pooled analyses of placebo-controlled trials in adults with MDD or other psychiatric disorders included a total of 295 short-term trials (median duration of 2 months) of 11 antidepressant drugs in over 77,000 patients. There was considerable variation in risk of suicidality among drugs, but a tendency toward an increase in the younger patients for almost all drugs studied. There were differences in absolute risk of suicidality across the different indications, with the highest incidence in MDD. The risk differences (drug vs placebo), however, were relatively stable within age strata and across indications. These risk differences (drug-placebo difference in the number of cases of suicidality per 1,000 patients treated) are provided in Table 1.

Table 1
Age Range | Drug-Placebo Difference in; Number of Cases of Suicidality; per 1,000 Patients Treated
 | Increases Compared to Placebo
<18 | 14 additional cases
18-24 | 5 additional cases
 | Decreases Compared to Placebo
25-64 | 1 fewer case
≥65 | 6 fewer cases

No suicides occurred in any of the pediatric trials. There were suicides in the adult trials, but the number was not sufficient to reach any conclusion about drug effect on suicide.

It is unknown whether the suicidality risk extends to longer-term use, i.e., beyond several months. However, there is substantial evidence from placebo-controlled maintenance trials in adults with depression that the use of antidepressants can delay the recurrence of depression.

All patients being treated with antidepressants for any indication should be monitored appropriately and observed closely for clinical worsening, suicidality, and unusual changes in behavior, especially during the initial few months of a course of drug therapy, or at times of dose changes, either increases or decreases.

The following symptoms, anxiety, agitation, panic attacks, insomnia, irritability, hostility, aggressiveness, impulsivity, akathisia (psychomotor restlessness), hypomania, and mania, have been reported in adult and pediatric patients being treated with antidepressants for major depressive disorder as well as for other indications, both psychiatric and nonpsychiatric. Although a causal link between the emergence of such symptoms and either the worsening of depression and/or the emergence of suicidal impulses has not been established, there is concern that such symptoms may represent precursors to emerging suicidality.

Consideration should be given to changing the therapeutic regimen, including possibly discontinuing the medication, in patients whose depression is persistently worse, or who are experiencing emergent suicidality or symptoms that might be precursors to worsening depression or suicidality, especially if these symptoms are severe, abrupt in onset, or were not part of the patient’s presenting symptoms.

Families and caregivers of patients being treated with antidepressants for major depressive disorder or other indications, both psychiatric and nonpsychiatric, should be alerted about the need to monitor patients for the emergence of agitation, irritability, unusual changes in behavior, and the other symptoms described above, as well as the emergence of suicidality, and to report such symptoms immediately to healthcare providers. Such monitoring should include daily observation by families and caregivers. Prescriptions for bupropion hydrochloride should be written for the smallest quantity of tablets consistent with good patient management, in order to reduce the risk of overdose.

Neuropsychiatric Symptoms and Suicide Risk in Smoking Cessation Treatment

Bupropion hydrochloride, bupropion hydrochloride, the sustained-release formulation, and bupropion hydrochloride, the extended-release formulation, are not approved for smoking cessation treatment, but bupropion under the name ZYBAN (bupropion hydrochloride) Sustained-Release Tablets is approved for this use. Serious neuropsychiatric symptoms have been reported in patients taking bupropion for smoking cessation (see BOXED WARNING, ADVERSE REACTIONS). These have included changes in mood (including depression and mania), psychosis, hallucinations, paranoia, delusions, homicidal ideation, hostility, agitation, aggression, anxiety, and panic, as well as suicidal ideation, suicide attempt, and completed suicide. Some reported cases may have been complicated by the symptoms of nicotine withdrawal in patients who stopped smoking. Depressed mood may be a symptom of nicotine withdrawal. Depression, rarely including suicidal ideation, has been reported in smokers undergoing a smoking cessation attempt without medication. However, some of these symptoms have occurred in patients taking bupropion who continued to smoke. When symptoms were reported, most were during bupropion treatment, but some were following discontinuation of bupropion therapy.

These events have occurred in patients with and without pre-existing psychiatric disease; some have experienced worsening of their psychiatric illnesses. All patients being treated with bupropion as part of smoking cessation treatment should be observed for neuropsychiatric symptoms or worsening of pre-existing psychiatric illness.

Patients with serious psychiatric illness such as schizophrenia, bipolar disorder, and major depressive disorder did not participate in the pre-marketing studies of ZYBAN.

Advise patients and caregivers that the patient using bupropion for smoking cessation should stop taking bupropion and contact a healthcare provider immediately if agitation, depressed mood, or changes in behavior or thinking that are not typical for the patient are observed, or if the patient develops suicidal ideation or suicidal behavior. In many postmarketing cases, resolution of symptoms after discontinuation of ZYBAN was reported, although in some cases the symptoms persisted, therefore, ongoing monitoring and supportive care should be provided until symptoms resolve.

The risks of using bupropion for smoking cessation should be weighed against the benefits of its use. ZYBAN has been demonstrated to increase the likelihood of abstinence from smoking for as long as six months compared to treatment with placebo. The health benefits of quitting smoking are immediate and substantial.

Screening Patients for Bipolar Disorder

A major depressive episode may be the initial presentation of bipolar disorder. It is generally believed (though not established in controlled trials) that treating such an episode with an antidepressant alone may increase the likelihood of precipitation of a mixed/manic episode in patients at risk for bipolar disorder. Whether any of the symptoms described above represent such a conversion is unknown. However, prior to initiating treatment with an antidepressant, patients with depressive symptoms should be adequately screened to determine if they are at risk for bipolar disorder; such screening should include a detailed psychiatric history, including a family history of suicide, bipolar disorder, and depression. It should be noted that bupropion hydrochloride tablets are not approved for use in treating bipolar depression.

Bupropion-Containing Products

Patients should be made aware that bupropion hydrochloride tablets contain the same active ingredient found in ZYBAN, used as an aid to smoking cessation treatment, and that bupropion hydrochloride tablets should not be used in combination with ZYBAN, or any other medications that contain bupropion, such as Wellbutrin SR (bupropion hydrochloride), the sustained-release formulation or Wellbutrin XL (bupropion hydrochloride), the extended-release formulation.

Seizures

Bupropion is associated with seizures in approximately 0.4% (4/1,000) of patients treated at doses up to 450 mg/day. This incidence of seizures may exceed that of other marketed antidepressants by as much as 4-fold. This relative risk is only an approximate estimate because no direct comparative studies have been conducted. The estimated seizure incidence for bupropion hydrochloride tablets increases almost tenfold between 450 and 600 mg/day, which is twice the usually required daily dose (300 mg) and one and one-third the maximum recommended daily dose (450 mg). Given the wide variability among individuals and their capacity to metabolize and eliminate drugs this disproportionate increase in seizure incidence with dose incrementation calls for caution in dosing.

During the initial development, 25 among approximately 2,400 patients treated with bupropion hydrochloride tablets experienced seizures. At the time of seizure, 7 patients were receiving daily doses of 450 mg or below for an incidence of 0.33% (3/1,000) within the recommended dose range. Twelve patients experienced seizures at 600 mg/day (2.3% incidence); 6 additional patients had seizures at daily doses between 600 and 900 mg (2.8% incidence).

A separate, prospective study was conducted to determine the incidence of seizure during an 8-week treatment exposure in approximately 3,200 additional patients who received daily doses of up to 450 mg. Patients were permitted to continue treatment beyond 8 weeks if clinically indicated. Eight seizures occurred during the initial 8-week treatment period and 5 seizures were reported in patients continuing treatment beyond 8 weeks, resulting in a total seizure incidence of 0.4%.

The risk of seizure appears to be strongly associated with dose. Sudden and large increments in dose may contribute to increased risk. While many seizures occurred early in the course of treatment, some seizures did occur after several weeks at fixed dose. Bupropion hydrochloride tablets should be discontinued and not restarted in patients who experience a seizure while on treatment.

The risk of seizure is also related to patient factors, clinical situations, and concomitant medications, which must be considered in selection of patients for therapy with bupropion hydrochloride tablets.

- Patient factors: Predisposing factors that may increase the risk of seizure with bupropion use include history of head trauma or prior seizure, central nervous system (CNS) tumor, the presence of severe hepatic cirrhosis, and concomitant medications that lower seizure threshold.
- Clinical situations: Circumstances associated with an increased seizure risk include, among others, excessive use of alcohol or sedatives (including benzodiazepines); addiction to opiates, cocaine, or stimulants; use of over-the-counter stimulants and anorectics; and diabetes treated with oral hypoglycemics or insulin.
- Concomitant medications: Many medications (e.g., antipsychotics, antidepressants, theophylline, systemic steroids) are known to lower seizure threshold.

Recommendations for Reducing the Risk of Seizure

Retrospective analysis of clinical experience gained during the development of bupropion hydrochloride tablets suggests that the risk of seizure may be minimized if

- the total daily dose of bupropion hydrochloride tablets does not exceed 450 mg,
- the daily dose is administered 3 times daily, with each single dose not to exceed 150 mg to avoid high peak concentrations of bupropion and/or its metabolites, and
- the rate of incrementation of dose is very gradual.

Bupropion hydrochloride tablets should be administered with extreme caution to patients with a history of seizure, cranial trauma, or other predisposition(s) toward seizure, or patients treated with other agents (e.g., antipsychotics, other antidepressants, theophylline, systemic steroids, etc.) that lower seizure threshold.

Hepatic Impairment

Bupropion hydrochloride tablets should be used with extreme caution in patients with severe hepatic cirrhosis. In these patients a reduced dose and/or frequency is required, as peak bupropion, as well as AUC, levels are substantially increased and accumulation is likely to occur in such patients to a greater extent than usual. The dose should not exceed 75 mg once a day in these patients (see CLINICAL PHARMACOLOGY, PRECAUTIONS, and DOSAGE AND ADMINISTRATION).

Potential for Hepatotoxicity

In rats receiving large doses of bupropion chronically, there was an increase in incidence of hepatic hyperplastic nodules and hepatocellular hypertrophy. In dogs receiving large doses of bupropion chronically, various histologic changes were seen in the liver, and laboratory tests suggesting mild hepatocellular injury were noted.

PRECAUTIONS

General

Agitation and Insomnia

A substantial proportion of patients treated with bupropion hydrochloride tablets experience some degree of increased restlessness, agitation, anxiety, and insomnia, especially shortly after initiation of treatment. In clinical studies, these symptoms were sometimes of sufficient magnitude to require treatment with sedative/hypnotic drugs. In approximately 2% of patients, symptoms were sufficiently severe to require discontinuation of treatment with bupropion hydrochloride tablets.

Psychosis, Confusion, and Other Neuropsychiatric Phenomena

Depressed patients treated with bupropion hydrochloride tablets have been reported to show a variety of neuropsychiatric signs and symptoms including delusions, hallucinations, psychosis, concentration disturbance, paranoia, and confusion. Because of the uncontrolled nature of many studies, it is impossible to provide a precise estimate of the extent of risk imposed by treatment with bupropion hydrochloride tablets. In several cases, neuropsychiatric phenomena abated upon dose reduction and/or withdrawal of treatment.

Activation of Psychosis and/or Mania

Antidepressants can precipitate manic episodes in bipolar disorder patients during the depressed phase of their illness and may activate latent psychosis in other susceptible patients. Bupropion hydrochloride tablets are expected to pose similar risks.

Altered Appetite and Weight

A weight loss of greater than 5 lbs occurred in 28% of patients receiving bupropion hydrochloride tablets. This incidence is approximately double that seen in comparable patients treated with tricyclics or placebo. Furthermore, while 35% of patients receiving tricyclic antidepressants gained weight, only 9.4% of patients treated with bupropion did. Consequently, if weight loss is a major presenting sign of a patient’s depressive illness, the anorectic and/or weight reducing potential of bupropion hydrochloride tablets should be considered.

Allergic Reactions

Anaphylactoid/anaphylactic reactions characterized by symptoms such as pruritus, urticaria, angioedema, and dyspnea requiring medical treatment have been reported in clinical trials with bupropion. In addition, there have been rare spontaneous postmarketing reports of erythema multiforme, Stevens-Johnson syndrome, and anaphylactic shock associated with bupropion. A patient should stop taking bupropion hydrochloride tablets and consult a doctor if experiencing allergic or anaphylactoid/anaphylactic reactions (e.g., skin rash, pruritus, hives, chest pain, edema, and shortness of breath) during treatment.

Arthralgia, myalgia, and fever with rash and other symptoms suggestive of delayed hypersensitivity have been reported in association with bupropion. These symptoms may resemble serum sickness.

Cardiovascular Effects

In clinical practice, hypertension, in some cases severe, requiring acute treatment, has been reported in patients receiving bupropion alone and in combination with nicotine replacement therapy. These events have been observed in both patients with and without evidence of preexisting hypertension.

Data from a comparative study of the sustained-release formulation of bupropion (ZYBAN Sustained-Release Tablets), nicotine transdermal system (NTS), the combination of sustained-release bupropion plus NTS, and placebo as an aid to smoking cessation suggest a higher incidence of treatment-emergent hypertension in patients treated with the combination of sustained-release bupropion and NTS. In this study, 6.1% of patients treated with the combination of sustained-release bupropion and NTS had treatment-emergent hypertension compared to 2.5%, 1.6%, and 3.1% of patients treated with sustained-release bupropion, NTS, and placebo, respectively. The majority of these patients had evidence of preexisting hypertension. Three patients (1.2%) treated with the combination of ZYBAN and NTS and one patient (0.4%) treated with NTS had study medication discontinued due to hypertension compared to none of the patients treated with ZYBAN or placebo. Monitoring of blood pressure is recommended in patients who receive the combination of bupropion and nicotine replacement.

There is no clinical experience establishing the safety of bupropion hydrochloride tablets in patients with a recent history of myocardial infarction or unstable heart disease. Therefore, care should be exercised if it is used in these groups. Bupropion was well tolerated in depressed patients who had previously developed orthostatic hypotension while receiving tricyclic antidepressants and was also generally well tolerated in a group of 36 depressed inpatients with stable congestive heart failure (CHF). However, bupropion was associated with a rise in supine blood pressure in the study of patients with CHF, resulting in discontinuation of treatment in 2 patients for exacerbation of baseline hypertension.

Hepatic Impairment

Bupropion hydrochloride tablets should be used with extreme caution in patients with severe hepatic cirrhosis. In these patients, a reduced dose and frequency is required. Bupropion hydrochloride tablets should be used with caution in patients with hepatic impairment (including mild-to-moderate hepatic cirrhosis) and a reduced frequency and/or dose should be considered in patients with mild-to-moderate hepatic cirrhosis.

All patients with hepatic impairment should be closely monitored for possible adverse effects that could indicate high drug and metabolite levels (see CLINICAL PHARMACOLOGY, WARNINGS, and DOSAGE AND ADMINISTRATION).

Renal Impairment

There is limited information on the pharmacokinetics of bupropion in patients with renal impairment. An inter-study comparison between normal subjects and patients with end-stage renal failure demonstrated that the parent drug Cmax and AUC values were comparable in the 2 groups, whereas the hydroxybupropion and threohydrobupropion metabolites had a 2.3- and 2.8-fold increase, respectively, in AUC for patients with end-stage renal failure. A second study, comparing normal subjects and patients with moderate-to-severe renal impairment (GFR 30.9 ± 10.8 mL/min) showed that exposure to a single 150 mg dose of sustained-release bupropion was approximately 2-fold higher in patients with impaired renal function while levels of the hydroxybupropion and threo/erythrohydrobupropion (combined) metabolites were similar in the 2 groups. Bupropion is extensively metabolized in the liver to active metabolites, which are further metabolized and subsequently excreted by the kidneys. Bupropion hydrochloride tablets should be used with caution in patients with renal impairment and a reduced frequency and/or dose should be considered as bupropion and the metabolites of bupropion may accumulate in such patients to a greater extent than usual. The patient should be closely monitored for possible adverse effects that could indicate high drug or metabolite levels.

Information for Patients

Prescribers or other health professionals should inform patients, their families, and their caregivers about the benefits and risks associated with treatment with bupropion hydrochloride and should counsel them in its appropriate use. A patient Medication Guide about “Antidepressant Medicines, Depression and Other Serious Mental Illnesses, and Suicidal Thoughts or Actions,” “Quitting Smoking, Quit-Smoking Medication, Changes in Thinking and Behavior, Depression, and Suicidal Thoughts or Actions,” and “What Other Important Information Should I Know About Bupropion Hydrochloride Tablets?” is available for bupropion hydrochloride tablets. The prescriber or health professional should instruct patients, their families, and their caregivers to read the Medication Guide and should assist them in understanding its contents. Patients should be given the opportunity to discuss the contents of the Medication Guide and to obtain answers to any questions they may have. The complete text of the Medication Guide is reprinted at the end of this document.

Patients should be advised of the following issues and asked to alert their prescriber if these occur while taking bupropion hydrochloride.

Clinical Worsening and Suicide Risk in Treating Psychiatric Disorders

Patients, their families, and their caregivers should be encouraged to be alert to the emergence of anxiety, agitation, panic attacks, insomnia, irritability, hostility, aggressiveness, impulsivity, akathisia (psychomotor restlessness), hypomania, mania, other unusual changes in behavior, worsening of depression, and suicidal ideation, especially early during antidepressant treatment and when the dose is adjusted up or down. Families and caregivers of patients should be advised to look for the emergence of such symptoms on a day-to-day basis, since changes may be abrupt. Such symptoms should be reported to the patient’s prescriber or health professional, especially if they are severe, abrupt in onset, or were not part of the patient’s presenting symptoms. Symptoms such as these may be associated with an increased risk for suicidal thinking and behavior and indicate a need for very close monitoring and possibly changes in the medication.

Neuropsychiatric Symptoms and Suicide Risk in Smoking Cessation Treatment

Although bupropion hydrochloride tablets are not indicated for smoking cessation treatment, it contains the same active ingredient as ZYBAN which is approved for this use. Patients should be informed that quitting smoking, with or without ZYBAN, may be associated with nicotine withdrawal symptoms (including depression or agitation), or exacerbation of pre-existing psychiatric illness. Furthermore, some patients have experienced changes in mood (including depression and mania), psychosis, hallucinations, paranoia, delusions, homicidal ideation aggression, anxiety, and panic, as well as suicidal ideation, suicide attempt, and completed suicide when attempting to quit smoking while taking ZYBAN. If patients develop agitation, hostility, depressed mood, or changes in thinking or behavior that are not typical for them, or if patients develop suicidal ideation or behavior, they should be urged to report these symptoms to their healthcare provider immediately.

Bupropion-Containing Products

Patients should be made aware that bupropion hydrochloride tablets contain the same active ingredient found in ZYBAN, used as an aid to smoking cessation, and that bupropion hydrochloride tablets should not be used in combination with ZYBAN or any other medications that contain bupropion hydrochloride (such as Wellbutrin SR, the sustained-release formulation and Wellbutrin XL, the extended-release formulation).

Patients should be instructed to take bupropion hydrochloride tablets in equally divided doses 3 or 4 times a day to minimize the risk of seizure.

Patients should be told that bupropion hydrochloride tablets should be discontinued and not restarted if they experience a seizure while on treatment.

Patients should be told that any CNS-active drug like bupropion hydrochloride tablets may impair their ability to perform tasks requiring judgment or motor and cognitive skills. Consequently, until they are reasonably certain that bupropion hydrochloride tablets do not adversely affect their performance, they should refrain from driving an automobile or operating complex, hazardous machinery.

Patients should be told that the excessive use or abrupt discontinuation of alcohol or sedatives (including benzodiazepines) may alter the seizure threshold. Some patients have reported lower alcohol tolerance during treatment with bupropion hydrochloride tablets. Patients should be advised that the consumption of alcohol should be minimized or avoided.

Patients should be advised to inform their physicians if they are taking or plan to take any prescription or over-the-counter drugs. Concern is warranted because bupropion hydrochloride tablets and other drugs may affect each other’s metabolism.

Patients should be advised to notify their physicians if they become pregnant or intend to become pregnant during therapy.

Laboratory Tests

There are no specific laboratory tests recommended.

Drug Interactions

Because bupropion is extensively metabolized, the coadministration of other drugs may affect its clinical activity. In vitro studies indicate that bupropion is primarily metabolized to hydroxybupropion by the CYP2B6 isoenzyme. Therefore, the potential exists for a drug interaction between bupropion hydrochloride tablets and drugs that are substrates of or inhibitors/inducers of the CYP2B6 isoenzyme (e.g., orphenadrine, thiotepa, cyclophosphamide, ticlopidine, and clopidogrel). In addition, in vitro studies suggest that paroxetine, sertraline, norfluoxetine, and fluvoxamine as well as nelfinavir inhibit the hydroxylation of bupropion. No clinical studies have been performed to evaluate this finding. The threohydrobupropion metabolite of bupropion does not appear to be produced by the cytochrome P450 isoenzymes. The effects of concomitant administration of cimetidine on the pharmacokinetics of bupropion and its active metabolites were studied in 24 healthy young male volunteers. Following oral administration of two 150 mg sustained-release tablets with and without 800 mg of cimetidine, the pharmacokinetics of bupropion and hydroxybupropion were unaffected. However, there were 16% and 32% increases in the AUC and Cmax, respectively, of the combined moieties of threohydrobupropion and erythrohydrobupropion.

In a series of studies in healthy volunteers, ritonavir (100 mg twice daily or 600 mg twice daily) or ritonavir 100 mg plus lopinavir 400 mg (KALETRA) twice daily reduced the exposure of bupropion and its major metabolites in a dose dependent manner by approximately 20% to 80%. Similarly, efavirenz 600 mg once daily for 2 weeks reduced the exposure of bupropion by approximately 55%. This effect of ritonavir, KALETRA, and efavirenz is thought to be due to the induction of bupropion metabolism. Patients receiving any of these drugs with bupropion may need increased doses of bupropion, but the maximum recommended dose of bupropion should not be exceeded (see CLINICAL PHARMACOLOGY: Metabolism).

While not systematically studied, certain drugs may induce the metabolism of bupropion (e.g., carbamazepine, phenobarbital, phenytoin).

Multiple oral doses of bupropion had no statistically significant effects on the single dose pharmacokinetics of lamotrigine in 12 healthy volunteers.

Animal data indicated that bupropion may be an inducer of drug-metabolizing enzymes in humans. In one study, following chronic administration of bupropion, 100 mg 3 times daily to 8 healthy male volunteers for 14 days, there was no evidence of induction of its own metabolism. Nevertheless, there may be the potential for clinically important alterations of blood levels of coadministered drugs.

Drugs Metabolized by Cytochrome P450IID6 (CYP2D6)

Many drugs, including most antidepressants (SSRIs, many tricyclics), beta-blockers, antiarrhythmics, and antipsychotics are metabolized by the CYP2D6 isoenzyme. Although bupropion is not metabolized by this isoenzyme, bupropion and hydroxybupropion are inhibitors of the CYP2D6 isoenzyme in vitro. In a study of 15 male subjects (ages 19 to 35 years) who were extensive metabolizers of the CYP2D6 isoenzyme, daily doses of bupropion given as 150 mg twice daily followed by a single dose of 50 mg desipramine increased the Cmax, AUC, and t1/2 of desipramine by an average of approximately 2-, 5- and 2-fold, respectively. The effect was present for at least 7 days after the last dose of bupropion. Concomitant use of bupropion with other drugs metabolized by CYP2D6 has not been formally studied.

Therefore, co-administration of bupropion with drugs that are metabolized by CYP2D6 isoenzyme including certain antidepressants (e.g., nortriptyline, imipramine, desipramine, paroxetine, fluoxetine, sertraline), antipsychotics (e.g., haloperidol, risperidone, thioridazine), beta-blockers (e.g., metoprolol), and Type 1C antiarrhythmics (e.g., propafenone, flecainide), should be approached with caution and should be initiated at the lower end of the dose range of the concomitant medication. If bupropion is added to the treatment regimen of a patient already receiving a drug metabolized by CYP2D6, the need to decrease the dose of the original medication should be considered, particularly for those concomitant medications with a narrow therapeutic index.

Drugs which require metabolic activation by CYP2D6 in order to be effective (e.g., tamoxifen) theoretically could have reduced efficacy when administered concomitantly with inhibitors of CYP2D6 such as bupropion.

Although citalopram is not primarily metabolized by CYP2D6, in one study bupropion increased the Cmax and AUC of citalopram by 30% and 40%, respectively. Citalopram did not affect the pharmacokinetics of bupropion and its 3 metabolites.

MAO Inhibitors

Concomitant use of MAOIs and bupropion is contraindicated. Bupropion inhibits the reuptake of dopamine and norepinephrine and can increase risk of hypertensive reactions when used concomitantly with drugs that also inhibit the reuptake of dopamine or norepinephrine, including MAOIs. In addition, MAOIs decrease the metabolism of dopamine and norepinephrine. These effects can increase dopaminergic and noradrenergic activity. Studies in animals demonstrate that the acute toxicity of bupropion is enhanced by the MAO inhibitor phenelzine (see CONTRAINDICATIONS and DOSAGE AND ADMINISTRATION).

Levodopa and Amantadine

Limited clinical data suggest a higher incidence of adverse experiences in patients receiving bupropion concurrently with either levodopa or amantadine. Administration of bupropion hydrochloride tablets to patients receiving either levodopa or amantadine concurrently should be undertaken with caution, using small initial doses and small gradual dose increases.

Drugs that Lower Seizure Threshold

Concurrent administration of bupropion hydrochloride tablets and agents (e.g., antipsychotics, other antidepressants, theophylline, systemic steroids, etc.) that lower seizure threshold should be undertaken only with extreme caution (see WARNINGS). Low initial dosing and small gradual dose increases should be employed.

Nicotine Transdermal System

(See PRECAUTIONS: Cardiovascular Effects)

Alcohol

In post-marketing experience, there have been rare reports of adverse neuropsychiatric events or reduced alcohol tolerance in patients who were drinking alcohol during treatment with bupropion hydrochloride tablets. The consumption of alcohol during treatment with bupropion hydrochloride tablets should be minimized or avoided (also see CONTRAINDICATIONS).

Drug-Laboratory Test Interactions

False-positive urine immunoassay screening tests for amphetamines have been reported in patients taking bupropion. This is due to lack of specificity of some screening tests. False-positive test results may result even following discontinuation of bupropion therapy. Confirmatory tests, such as gas chromatography/mass spectrometry, will distinguish bupropion from amphetamines.

Carcinogenesis, Mutagenesis, Impairment of Fertility

Lifetime carcinogenicity studies were performed in rats and mice at doses up to 300 and 150 mg/kg/day, respectively. In the rat study there was an increase in nodular proliferative lesions of the liver at doses of 100 to 300 mg/kg/day; lower doses were not tested. The question of whether or not such lesions may be precursors of neoplasms of the liver is currently unresolved. Similar liver lesions were not seen in the mouse study, and no increase in malignant tumors of the liver and other organs was seen in either study.

Bupropion produced a borderline positive response (2 to 3 times control mutation rate) in some strains in the Ames bacterial mutagenicity test, and a high oral dose (300 mg/kg, but not 100 or 200 mg/kg) produced a low incidence of chromosomal aberrations in rats. The relevance of these results in estimating the risk of human exposure to therapeutic doses is unknown.

A fertility study was performed in rats; no evidence of impairment of fertility was encountered at oral doses up to 300 mg/kg/day.

Pregnancy

Teratogenic Effects

Pregnancy Category C

In studies conducted in rats and rabbits, bupropion was administered orally at doses up to 450 and 150 mg/kg/day, respectively (approximately 11 and 7 times the maximum recommended human dose [MRHD], respectively, on a mg/m^2 basis), during the period of organogenesis. No clear evidence of teratogenic activity was found in either species; however, in rabbits, slightly increased incidences of fetal malformations and skeletal variations were observed at the lowest dose tested (25 mg/kg/day, approximately equal to the MRHD on a mg/m^2 basis) and greater. Decreased fetal weights were seen at 50 mg/kg and greater.

When rats were administered bupropion at oral doses of up to 300 mg/kg/day (approximately 7 times the MRHD on a mg/m^2 basis) prior to mating and throughout pregnancy and lactation, there were no apparent adverse effects on offspring development.

One study has been conducted in pregnant women. This retrospective, managed-care database study assessed the risk of congenital malformations overall and cardiovascular malformations specifically, following exposure to bupropion in the first trimester compared to the risk of these malformations following exposure to other antidepressants in the first trimester and bupropion outside of the first trimester. This study included 7,005 infants with antidepressant exposure during pregnancy, 1,213 of whom were exposed to bupropion in the first trimester. The study showed no greater risk for congenital malformations overall or cardiovascular malformations specifically, following first trimester bupropion exposure compared to exposure to all other antidepressants in the first trimester, or bupropion outside of the first trimester. The results of this study have not been corroborated. Bupropion hydrochloride tablets should be used during pregnancy only if the potential benefit justifies the potential risk to the fetus.

Labor and Delivery

The effect of bupropion hydrochloride tablets on labor and delivery in humans is unknown.

Nursing Mothers

Like many other drugs, bupropion and its metabolites are secreted in human milk. Because of the potential for serious adverse reactions in nursing infants from bupropion, a decision should be made whether to discontinue nursing or to discontinue the drug, taking into account the importance of the drug to the mother.

Pediatric Use

Safety and effectiveness in the pediatric population have not been established (see BOX WARNING and WARNINGS: Clinical Worsening and Suicide Risk in Treating Psychiatric Disorders). Anyone considering the use of bupropion hydrochloride tablets in a child or adolescent must balance the potential risks with the clinical need.

Geriatric Use

Of the approximately 6,000 patients who participated in clinical trials with bupropion sustained-release tablets (depression and smoking cessation studies), 275 were 65 and over and 47 were 75 and over. In addition, several hundred patients 65 and over participated in clinical trials using the immediate-release formulation of bupropion (depression studies). No overall differences in safety or effectiveness were observed between these subjects and younger subjects, and other reported clinical experience has not identified differences in responses between the elderly and younger patients, but greater sensitivity of some older individuals cannot be ruled out.

A single-dose pharmacokinetic study demonstrated that the disposition of bupropion and its metabolites in elderly subjects was similar to that of younger subjects; however, another pharmacokinetic study, single and multiple dose, has suggested that the elderly are at increased risk for accumulation of bupropion and its metabolites (see CLINICAL PHARMACOLOGY).

Bupropion is extensively metabolized in the liver to active metabolites, which are further metabolized and excreted by the kidneys. The risk of toxic reaction to this drug may be greater in patients with impaired renal function. Because elderly patients are more likely to have decreased renal function, care should be taken in dose selection, and it may be useful to monitor renal function (see PRECAUTIONS: Renal Impairment and DOSAGE AND ADMINISTRATION).

ADVERSE REACTIONS

(See also WARNINGS and PRECAUTIONS)

Adverse events commonly encountered in patients treated with bupropion hydrochloride tablets are agitation, dry mouth, insomnia, headache/migraine, nausea/vomiting, constipation, and tremor.

Adverse events were sufficiently troublesome to cause discontinuation of treatment with bupropion hydrochloride tablets in approximately 10% of the 2,400 patients and volunteers who participated in clinical trials during the product’s initial development. The more common events causing discontinuation include neuropsychiatric disturbances (3.0%), primarily agitation and abnormalities in mental status; gastrointestinal disturbances (2.1%), primarily nausea and vomiting; neurological disturbances (1.7%), primarily seizures, headaches, and sleep disturbances; and dermatologic problems (1.4%), primarily rashes. It is important to note, however, that many of these events occurred at doses that exceed the recommended daily dose.

Accurate estimates of the incidence of adverse events associated with the use of any drug are difficult to obtain. Estimates are influenced by drug dose, detection technique, setting, physician judgments, etc. Consequently, Table 2 is presented solely to indicate the relative frequency of adverse events reported in representative controlled clinical studies conducted to evaluate the safety and efficacy of bupropion hydrochloride tablets under relatively similar conditions of daily dosage (300 to 600 mg), setting, and duration (3 to 4 weeks). The figures cited cannot be used to predict precisely the incidence of untoward events in the course of usual medical practice where patient characteristics and other factors must differ from those which prevailed in the clinical trials. These incidence figures also cannot be compared with those obtained from other clinical studies involving related drug products as each group of drug trials is conducted under a different set of conditions.

Finally, it is important to emphasize that the tabulation does not reflect the relative severity and/or clinical importance of the events. A better perspective on the serious adverse events associated with the use of bupropion hydrochloride tablets is provided in WARNINGS and PRECAUTIONS.

Table 2. Treatment-Emergent Adverse Experience Incidence in Placebo-Controlled Clinical Trials [Events reported by at least 1% of patients receiving bupropion hydrochloride tablets are included.] (Percent of Patients Reporting)
Adverse Experience | Bupropion Hydrochloride Tablets Patients (n = 323) | Placebo Patients (n = 185)
CARDIOVASCULAR
Cardiac arrhythmias | 5.3 | 4.3
Dizziness | 22.3 | 16.2
Hypertension | 4.3 | 1.6
Hypotension | 2.5 | 2.2
Palpitations | 3.7 | 2.2
Syncope | 1.2 | 0.5
Tachycardia | 10.8 | 8.6
DERMATOLOGIC
Pruritus | 2.2 | 0.0
Rash | 8.0 | 6.5
GASTROINTESTINAL
Anorexia | 18.3 | 18.4
Appetite increase | 3.7 | 2.2
Constipation | 26.0 | 17.3
Diarrhea | 6.8 | 8.6
Dyspepsia | 3.1 | 2.2
Nausea/vomiting | 22.9 | 18.9
Weight gain | 13.6 | 22.7
Weight loss | 23.2 | 23.2
GENITOURINARY
Impotence | 3.4 | 3.1
Menstrual complaints | 4.7 | 1.1
Urinary frequency | 2.5 | 2.2
Urinary retention | 1.9 | 2.2
MUSCULOSKELETAL
Arthritis | 3.1 | 2.7
NEUROLOGICAL
Akathisia | 1.5 | 1.1
Akinesia/bradykinesia | 8.0 | 8.6
Cutaneous temperature disturbance | 1.9 | 1.6
Dry mouth | 27.6 | 18.4
Excessive sweating | 22.3 | 14.6
Headache/migraine | 25.7 | 22.2
Impaired sleep quality | 4.0 | 1.6
Increased salivary flow | 3.4 | 3.8
Insomnia | 18.6 | 15.7
Muscle spasms | 1.9 | 3.2
Pseudoparkinsonism | 1.5 | 1.6
Sedation | 19.8 | 19.5
Sensory disturbance | 4.0 | 3.2
Tremor | 21.1 | 7.6
NEUROPSYCHIATRIC
Agitation | 31.9 | 22.2
Anxiety | 3.1 | 1.1
Confusion | 8.4 | 4.9
Decreased libido | 3.1 | 1.6
Delusions | 1.2 | 1.1
Disturbed concentration | 3.1 | 3.8
Euphoria | 1.2 | 0.5
Hostility | 5.6 | 3.8
NONSPECIFIC
Fatigue | 5.0 | 8.6
Fever/chills | 1.2 | 0.5
RESPIRATORY
Upper respiratory complaints | 5.0 | 11.4
SPECIAL SENSES
Auditory disturbance | 5.3 | 3.2
Blurred vision | 14.6 | 10.3
Gustatory disturbance | 3.1 | 1.1

Other Events Observed During the Development of Bupropion Hydrochloride Tablets

The conditions and duration of exposure to bupropion hydrochloride tablets varied greatly, and a substantial proportion of the experience was gained in open and uncontrolled clinical settings. During this experience, numerous adverse events were reported; however, without appropriate controls, it is impossible to determine with certainty which events were or were not caused by bupropion hydrochloride tablets. The following enumeration is organized by organ system and describes events in terms of their relative frequency of reporting in the data base. Events of major clinical importance are also described in WARNINGS and PRECAUTIONS.

The following definitions of frequency are used: Frequent adverse events are defined as those occurring in at least 1/100 patients. Infrequent adverse events are those occurring in 1/100 to 1/1,000 patients, while rare events are those occurring in less than 1/1,000 patients.

Cardiovascular

Frequent was edema; infrequent were chest pain, electrocardiogram (ECG) abnormalities (premature beats and nonspecific ST-T changes), and shortness of breath/dyspnea; rare were flushing, pallor, phlebitis, and myocardial infarction.

Dermatologic

Frequent were nonspecific rashes; infrequent were alopecia and dry skin; rare were change in hair color, hirsutism, and acne.

Endocrine

Infrequent was gynecomastia; rare were glycosuria and hormone level change.

Gastrointestinal

Infrequent were dysphagia, thirst disturbance, and liver damage/jaundice; rare were rectal complaints, colitis, gastrointestinal bleeding, intestinal perforation, and stomach ulcer.

Genitourinary

Frequent was nocturia; infrequent were vaginal irritation, testicular swelling, urinary tract infection, painful erection, and retarded ejaculation; rare were dysuria, enuresis, urinary incontinence, menopause, ovarian disorder, pelvic infection, cystitis, dyspareunia, and painful ejaculation.

Hematologic/Oncologic

Rare were lymphadenopathy, anemia, and pancytopenia.

Musculoskeletal

Rare was musculoskeletal chest pain.

Neurological

(See WARNINGS)

Frequent were ataxia/incoordination, seizure, myoclonus, dyskinesia, and dystonia; infrequent were mydriasis, vertigo, and dysarthria; rare were electroencephalogram (EEG) abnormality, abnormal neurological exam, impaired attention, sciatica, and aphasia.

Neuropsychiatric

(See PRECAUTIONS)

Frequent were mania/hypomania, increased libido, hallucinations, decrease in sexual function, and depression; infrequent were memory impairment, depersonalization, psychosis, dysphoria, mood instability, paranoia, formal thought disorder, and frigidity; rare was suicidal ideation.

Oral Complaints

Frequent was stomatitis; infrequent were toothache, bruxism, gum irritation, and oral edema; rare was glossitis.

Respiratory

Infrequent were bronchitis and shortness of breath/dyspnea; rare were epistaxis, rate or rhythm disorder, pneumonia, and pulmonary embolism.

Special Senses

Infrequent was visual disturbance; rare was diplopia.

Nonspecific

Frequent were flu-like symptoms; infrequent was nonspecific pain; rare were body odor, surgically related pain, infection, medication reaction, and overdose.

Postintroduction Reports

Voluntary reports of adverse events temporally associated with bupropion that have been received since market introduction and which may have no causal relationship with the drug include the following:

Body (General)

Arthralgia, myalgia, and fever with rash and other symptoms suggestive of delayed hypersensitivity. These symptoms may resemble serum sickness (see PRECAUTIONS).

Cardiovascular

Hypertension (in some cases severe, see PRECAUTIONS), orthostatic hypotension, third degree heart block

Endocrine

Syndrome of inappropriate antidiuretic hormone secretion, hyperglycemia, hypoglycemia

Gastrointestinal

Esophagitis, hepatitis, liver damage

Hemic and Lymphatic

Ecchymosis, leukocytosis, leukopenia, thrombocytopenia. Altered PT and/or INR, infrequently associated with hemorrhagic or thrombotic complications, were observed when bupropion was coadministered with warfarin.

Musculoskeletal

Arthralgia, myalgia, muscle rigidity/fever/rhabdomyolysis, muscle weakness

Nervous

Aggression, coma, completed suicide, delirium, dream abnormalities, paranoid ideation, paresthesia, restlessness, suicide attempt, unmasking of tardive dyskinesia

Skin and Appendages

Stevens-Johnson syndrome, angioedema, exfoliative dermatitis, urticaria

Special Senses

Tinnitus, increased intraocular pressure

DRUG ABUSE AND DEPENDENCE

Humans

Controlled clinical studies conducted in normal volunteers, in subjects with a history of multiple drug abuse, and in depressed patients showed some increase in motor activity and agitation/excitement.

In a population of individuals experienced with drugs of abuse, a single dose of 400 mg of bupropion hydrochloride tablets produced mild amphetamine-like activity as compared to placebo on the Morphine-Benzedrine Subscale of the Addiction Research Center Inventories (ARCI) and a score intermediate between placebo and amphetamine on the Liking Scale of the ARCI. These scales measure general feelings of euphoria and drug desirability.

Findings in clinical trials, however, are not known to predict the abuse potential of drugs reliably. Nonetheless, evidence from single-dose studies does suggest that the recommended daily dosage of bupropion when administered in divided doses is not likely to be especially reinforcing to amphetamine or stimulant abusers. However, higher doses that could not be tested because of the risk of seizure might be modestly attractive to those who abuse stimulant drugs.

Animals

Studies in rodents have shown that bupropion exhibits some pharmacologic actions common to psychostimulants including increases in locomotor activity and the production of a mild stereotyped behavior and increases in rates of responding in several schedule-controlled behavior paradigms. Drug discrimination studies in rats showed stimulus generalization between bupropion and amphetamine and other psychostimulants. Rhesus monkeys have been shown to self-administer bupropion intravenously.

OVERDOSAGE

Human Overdose Experience

Overdoses of up to 30 g or more of bupropion have been reported. Seizure was reported in approximately one-third of all cases. Other serious reactions reported with overdoses of bupropion alone included hallucinations, loss of consciousness, sinus tachycardia, and ECG changes such as conduction disturbances (including QRS prolongation) or arrhythmias. Fever, muscle rigidity, rhabdomyolysis, hypotension, stupor, coma, and respiratory failure have been reported mainly when bupropion was part of multiple drug overdoses.

Although most patients recovered without sequelae, deaths associated with overdoses of bupropion alone have been reported in patients ingesting large doses of the drug. Multiple uncontrolled seizures, bradycardia, cardiac failure, and cardiac arrest prior to death were reported in these patients.

Overdosage Management

Ensure an adequate airway, oxygenation, and ventilation. Monitor cardiac rhythm and vital signs. EEG monitoring is also recommended for the first 48 hours post-ingestion. General supportive and symptomatic measures are also recommended. Induction of emesis is not recommended.

Activated charcoal should be administered. There is no experience with the use of forced diuresis, dialysis, hemoperfusion, or exchange transfusion in the management of bupropion overdoses. No specific antidotes for bupropion are known.

Due to the dose-related risk of seizures with bupropion hydrochloride tablets, hospitalization following suspected overdose should be considered. Based on studies in animals, it is recommended that seizures be treated with intravenous benzodiazepine administration and other supportive measures, as appropriate.

In managing overdosage, consider the possibility of multiple drug involvement. The physician should consider contacting a poison control center for additional information on the treatment of any overdose. Telephone numbers for certified poison control centers are listed in the Physicians’ Desk Reference (PDR).

DOSAGE AND ADMINISTRATION

General Dosing Considerations

It is particularly important to administer bupropion hydrochloride tablets in a manner most likely to minimize the risk of seizure (see WARNINGS). Increases in dose should not exceed 100 mg/day in a 3-day period. Gradual escalation in dosage is also important if agitation, motor restlessness, and insomnia, often seen during the initial days of treatment, are to be minimized. If necessary, these effects may be managed by temporary reduction of dose or the short-term administration of an intermediate to long-acting sedative hypnotic. A sedative hypnotic usually is not required beyond the first week of treatment. Insomnia may also be minimized by avoiding bedtime doses. If distressing, untoward effects supervene, dose escalation should be stopped.

No single dose of bupropion hydrochloride tablets should exceed 150 mg. Bupropion hydrochloride tablets should be administered 3 times daily, preferably with at least 6 hours between successive doses.

Usual Dosage for Adults

The usual adult dose is 300 mg/day, given 3 times daily. Dosing should begin at 200 mg/day, given as 100 mg twice daily. Based on clinical response, this dose may be increased to 300 mg/day, given as 100 mg 3 times daily, no sooner than 3 days after beginning therapy (see Table 3).

Table 3. Dosing Regimen
Treatment Day | Total Daily Dose | Tablet Strength | Number of Tablets
 |  |  | Morning | Midday | Evening
1 | 200 mg | 100 mg | 1 | 0 | 1
4 | 300 mg | 100 mg | 1 | 1 | 1

Increasing the Dosage Above 300 mg/Day

As with other antidepressants, the full antidepressant effect of bupropion hydrochloride tablets may not be evident until 4 weeks of treatment or longer. An increase in dosage, up to a maximum of 450 mg/day, given in divided doses of not more than 150 mg each, may be considered for patients in whom no clinical improvement is noted after several weeks of treatment at 300 mg/day. Dosing above 300 mg/day may be accomplished using the 75 or 100 mg tablets. The 100 mg tablet must be administered 4 times daily with at least 4 hours between successive doses, in order not to exceed the limit of 150 mg in a single dose. Bupropion hydrochloride tablets should be discontinued in patients who do not demonstrate an adequate response after an appropriate period of treatment at 450 mg/day.

Maintenance Treatment

The lowest dose that maintains remission is recommended. Although it is not known how long the patient should remain on bupropion hydrochloride tablets, it is generally recognized that acute episodes of depression require several months or longer of antidepressant drug treatment.

Dosage Adjustment for Patients with Impaired Hepatic Function

Bupropion hydrochloride tablets should be used with extreme caution in patients with severe hepatic cirrhosis. The dose should not exceed 75 mg once a day in these patients. Bupropion hydrochloride tablets should be used with caution in patients with hepatic impairment (including mild-to-moderate hepatic cirrhosis) and a reduced frequency and/or dose should be considered in patients with mild-to-moderate hepatic cirrhosis (see CLINICAL PHARMACOLOGY, WARNINGS and PRECAUTIONS).

Dosage Adjustment for Patients with Impaired Renal Function

Bupropion hydrochloride tablets should be used with caution in patients with renal impairment and a reduced frequency and/or dose should be considered (see CLINICAL PHARMACOLOGY and PRECAUTIONS).

Switching a Patient To or From a Monoamine Oxidase Inhibitor (MAOI) Antidepressant

At least 14 days should elapse between discontinuation of an MAOI intended to treat depression and initiation of therapy with bupropion hydrochloride tablets. Conversely, at least 14 days should be allowed after stopping bupropion hydrochloride tablets before starting an MAOI antidepressant (see CONTRAINDICATIONS and Drug Interactions).

Use of Bupropion Hydrochloride Tablets With Reversible MAOIs Such as Linezolid or Methylene Blue

Do not start bupropion hydrochloride tablets in a patient who is being treated with a reversible MAOI such as linezolid or intravenous methylene blue. Drug interactions can increase the risk of hypertensive reactions. In a patient who requires more urgent treatment of a psychiatric condition, non-pharmacological interventions, including hospitalization, should be considered (see CONTRAINDICATIONS and Drug Interactions).

In some cases, a patient already receiving therapy with bupropion hydrochloride tablets may require urgent treatment with linezolid or intravenous methylene blue. If acceptable alternatives to linezolid or intravenous methylene blue treatment are not available and the potential benefits of linezolid or intravenous methylene blue treatment are judged to outweigh the risks of hypertensive reactions in a particular patient, bupropion hydrochloride tablets should be stopped promptly, and linezolid or intravenous methylene blue can be administered. The patient should be monitored for 2 weeks or until 24 hours after the last dose of linezolid or intravenous methylene blue, whichever comes first. Therapy with bupropion hydrochloride tablets may be resumed 24 hours after the last dose of linezolid or intravenous methylene blue.

The risk of administering methylene blue by non-intravenous routes (such as oral tablets or by local injection) or in intravenous doses much lower than 1 mg/kg with bupropion hydrochloride tablets is unclear. The clinician should, nevertheless, be aware of the possibility of a drug interaction with such use (see CONTRAINDICATIONS and Drug Interactions).

HOW SUPPLIED

Repackaged by Aphena Pharma Solutions - TN.
See Repackaging Information for available configurations.

Bupropion hydrochloride tablets, USP are supplied as:

75 mg: Lavender, round, film-coated tablets, debossed GG 929 on one side and plain on the reverse side.

NDC 0781-1053-31 in bottles of 30 tablets

NDC 0781-1053-01 in bottles of 100 tablets

NDC 0781-1053-10 in bottles of 1000 tablets

100 mg: Lavender, round, film-coated tablets, debossed GG 930 on one side and plain on the reverse side.

NDC 0781-1064-31 in bottles of 30 tablets

NDC 0781-1064-01 in bottles of 100 tablets

NDC 0781-1064-10 in bottles of 1000 tablets

STORAGE AND HANDLING

Store at 20º to 25ºC (68º to 77ºF) [see USP Controlled Room Temperature]. Protect from light and moisture.

Dispense in a tight, light-resistant container as defined in the USP.

MEDICATION GUIDE

BuPROPion Hydrochloride Tablets, USP

Read this Medication Guide carefully before you start using bupropion hydrochloride tablets and each time you get a refill. There may be new information. This information does not take the place of talking with your doctor about your medical condition or your treatment. If you have any questions about bupropion hydrochloride tablets, ask your doctor or pharmacist.

IMPORTANT: Be sure to read the three sections of this Medication Guide. The first section is about the risk of suicidal thoughts and actions with antidepressant medicines; the second section is about the risk of changes in thinking and behavior, depression and suicidal thoughts or actions with medicines used to quit smoking; and the third section is entitled “What Other Important Information Should I Know About Bupropion Hydrochloride Tablets?”

Antidepressant Medicines, Depression and Other Serious Mental Illnesses, and Suicidal Thoughts or Actions

This section of the Medication Guide is only about the risk of suicidal thoughts and actions with antidepressant medicines. Talk to your, or your family member’s healthcare provider about:

- all risks and benefits of treatment with antidepressant medicines
- all treatment choices for depression or other serious mental illness

What is the most important information I should know about antidepressant medicines, depression and other serious mental illnesses, and suicidal thoughts or actions?

1. Antidepressant medicines may increase suicidal thoughts or actions in some children, teenagers, and young adults within the first few months of treatment.
2. Depression and other serious mental illnesses are the most important causes of suicidal thoughts and actions. Some people may have a particularly high risk of having suicidal thoughts or actions. These include people who have (or have a family history of) bipolar illness (also called manic-depressive illness) or suicidal thoughts or actions.
3. How can I watch for and try to prevent suicidal thoughts and actions in myself or a family member?
  ∘ Pay close attention to any changes, especially sudden changes, in mood, behaviors, thoughts, or feelings. This is very important when an antidepressant medicine is started or when the dose is changed.
  ∘ Call the healthcare provider right away to report new or sudden changes in mood, behavior, thoughts, or feelings.
  ∘ Keep all follow-up visits with the healthcare provider as scheduled. Call the healthcare provider between visits as needed, especially if you have concerns about symptoms.

Call a healthcare provider right away if you or your family member has any of the following symptoms, especially if they are new, worse, or worry you:

- thoughts about suicide or dying
- attempts to commit suicide
- new or worse depression
- new or worse anxiety
- feeling very agitated or restless
- panic attacks
- trouble sleeping (insomnia)
- new or worse irritability
- acting aggressive, being angry, or violent
- acting on dangerous impulses
- an extreme increase in activity and talking (mania)
- other unusual changes in behavior or mood

What else do I need to know about antidepressant medicines?

- Never stop an antidepressant medicine without first talking to a healthcare provider. Stopping an antidepressant medicine suddenly can cause other symptoms.
- Antidepressants are medicines used to treat depression and other illnesses. It is important to discuss all the risks of treating depression and also the risks of not treating it. Patients and their families or other caregivers should discuss all treatment choices with the healthcare provider, not just the use of antidepressants.
- Antidepressant medicines have other side effects. Talk to the healthcare provider about the side effects of the medicine prescribed for you or your family member.
- Antidepressant medicines can interact with other medicines. Know all of the medicines that you or your family member takes. Keep a list of all medicines to show the healthcare provider. Do not start new medicines without first checking with your healthcare provider.
- Not all antidepressant medicines prescribed for children are FDA approved for use in children. Talk to your child’s healthcare provider for more information.

Bupropion hydrochloride tablets have not been studied in children under the age of 18 and are not approved for use in children and teenagers.

Quitting Smoking, Quit-Smoking Medications, Changes in Thinking and Behavior, Depression, and Suicidal Thoughts or Actions

This section of the Medication Guide is only about the risk of changes in thinking and behavior, depression and suicidal thoughts or actions with drugs used to quit smoking.

Although bupropion hydrochloride tablets is not a treatment for quitting smoking, it contains the same active ingredient (bupropion hydrochloride) as ZYBAN® which is used to help patients quit smoking.

Some people have had changes in behavior, hostility, agitation, depression, suicidal thoughts or actions while taking bupropion to help them quit smoking. These symptoms can develop during treatment with bupropion or after stopping treatment with bupropion.

If you, your family member, or your caregiver notice agitation, hostility, depression, or changes in thinking or behavior that are not typical for you, or you have any of the following symptoms, stop taking bupropion and call your healthcare provider right away:

- thoughts about suicide or dying
- attempts to commit suicide
- new or worse depression
- new or worse anxiety
- panic attacks
- feeling very agitated or restless
- acting aggressive, being angry, or violent
- acting on dangerous impulses
- an extreme increase in activity and talking (mania)
- abnormal thoughts or sensations
- seeing or hearing things that are not there (hallucinations)
- feeling people are against you (paranoia)
- feeling confused
- other unusual changes in behavior or mood

When you try to quit smoking, with or without bupropion, you may have symptoms that may be due to nicotine withdrawal, including urge to smoke, depressed mood, trouble sleeping, irritability, frustration, anger, feeling anxious, difficulty concentrating, restlessness, decreased heart rate, and increased appetite or weight gain. Some people have even experienced suicidal thoughts when trying to quit smoking without medication. Sometimes quitting smoking can lead to worsening of mental health problems that you already have, such as depression.

Before taking bupropion, tell your healthcare provider if you have ever had depression or other mental illnesses. You should also tell your doctor about any symptoms you had during other times you tried to quit smoking, with or without bupropion.

What other important information should I know about bupropion hydrochloride tablets?

- Seizures. There is a chance of having a seizure (convulsion, fit) with bupropion hydrochloride tablets, especially in people:
  ∘ with certain medical problems.
  ∘ who take certain medicines.
The chance of having seizures increases with higher doses of bupropion hydrochloride tablets. For more information, see the sections “Who should not take bupropion hydrochloride tablets?” and “What should I tell my doctor before using bupropion hydrochloride tablets?” Tell your doctor about all of your medical conditions and all the medicines you take. Do not take any other medicines while you are using bupropion hydrochloride tablets unless your doctor has said it is okay to take them.
If you have a seizure while taking bupropion hydrochloride tablets, stop taking the tablets and call your doctor right away. Do not take bupropion hydrochloride tablets again if you have a seizure.

- High blood pressure (hypertension). Some people get high blood pressure, that can be severe, while taking bupropion hydrochloride tablets. The chance of high blood pressure may be higher if you also use nicotine replacement therapy (such as a nicotine patch) to help you stop smoking.
- Severe allergic reactions. Some people have severe allergic reaction to bupropion hydrochloride tablets. Stop taking bupropion hydrochloride tablets and call your doctor right away if you get a rash, itching, hives, fever, swollen lymph glands, painful sores in the mouth or around the eyes, swelling of the lips or tongue, chest pain, or have trouble breathing. These could be signs of a serious allergic reaction.
- Unusual thoughts or behaviors. Some patients have unusual thoughts or behaviors while taking bupropion hydrochloride tablets, including delusions (believe you are someone else), hallucinations (seeing or hearing things that are not there), paranoia (feeling that people are against you), or feeling confused. If this happens to you, call your doctor.

What are bupropion hydrochloride tablets?

Bupropion hydrochloride tablets are a prescription medicine used to treat adults with a certain type of depression called major depressive disorder.

Who should not take bupropion hydrochloride tablets?

Do not take bupropion hydrochloride tablets if you

- have or had a seizure disorder or epilepsy.
- are taking ZYBAN (used to help people stop smoking) or any other medicines that contain bupropion hydrochloride, such as Wellbutrin SR Sustained-Release Tablets or Wellbutrin XL Extended-Release Tablets. Bupropion is the same active ingredient that is in bupropion hydrochloride tablets, USP.
- drink a lot of alcohol and abruptly stop drinking, or use medicines called sedatives (these make you sleepy) or benzodiazepines and you stop using them all of a sudden.
- take a monoamine oxidase inhibitor (MAOI). Ask your healthcare provider or pharmacist if you are not sure if you take an MAOI, including the antibiotic linezolid.
  - do not take an MAOI within 2 weeks of stopping bupropion hydrochloride tablets unless directed to do so by your physician.
  - do not start bupropion hydrochloride tablets if you stopped taking an MAOI in the last 2 weeks unless directed to do so by your physician.
- have or had an eating disorder such as anorexia nervosa or bulimia.
- are allergic to the active ingredient in bupropion hydrochloride tablets, bupropion, or to any of the inactive ingredients. See the end of this leaflet for a complete list of ingredients in bupropion hydrochloride tablets.

What should I tell my doctor before using bupropion hydrochloride tablets?

Tell your doctor if you have ever had depression, suicidal thoughts or actions, or other mental health problems. See “Antidepressant Medicines, Depression and Other Serious Mental Illnesses, and Suicidal Thoughts or Actions.”

- Tell your doctor about your other medical conditions including if you:
- are pregnant or plan to become pregnant. It is not known if bupropion hydrochloride tablets can harm your unborn baby.
- are breastfeeding. Bupropion hydrochloride tablets passes through your milk. It is not known if bupropion hydrochloride can harm your baby.
- have liver problems, especially cirrhosis of the liver.
- have kidney problems.
- have an eating disorder, such as anorexia nervosa or bulimia.
- have had a head injury.
- have had a seizure (convulsion, fit).
- have a tumor in your nervous system (brain or spine).
- have had a heart attack, heart problems, or high blood pressure.
- are a diabetic taking insulin or other medicines to control your blood sugar.
- drink a lot of alcohol.
- abuse prescription medicines or street drugs.
- Tell your doctor about all the medicines you take, including prescription and non-prescription medicines, vitamins, and herbal supplements. Many medicines increase your chances of having seizures or other serious side effects if you take them while you are using bupropion hydrochloride tablets.

How should I take bupropion hydrochloride tablets?

- Take bupropion hydrochloride tablets exactly as prescribed by your doctor.
- Take bupropion hydrochloride tablets at the same time each day.
- Take your doses of bupropion hydrochloride tablets at least 6 hours apart.
- You may take bupropion hydrochloride tablets with or without food.
- If you miss a dose, do not take an extra tablet to make up for the dose you forgot. Wait and take your next tablet at the regular time. This is very important. Too many bupropion hydrochloride tablets can increase your chance of having a seizure.
- If you take too many bupropion hydrochloride tablets, or overdose, call your local emergency room or poison control center right away.
- Do not take any other medicines while using bupropion hydrochloride tablets unless your doctor has told you it is okay.
- It may take several weeks for you to feel that bupropion hydrochloride tablets are working. Once you feel better, it is important to keep taking bupropion hydrochloride tablets exactly as directed by your doctor. Call your doctor if you do not feel bupropion hydrochloride tablets are working for you.
- Do not change your dose or stop taking bupropion hydrochloride tablets without talking with your doctor first.

What should I avoid while taking bupropion hydrochloride tablets?

- Do not drink a lot of alcohol while taking bupropion hydrochloride tablets. If you usually drink a lot of alcohol, talk with your doctor before suddenly stopping. If you suddenly stop drinking alcohol, you may increase your risk of having seizures.
- Do not drive a car or use heavy machinery until you know how bupropion hydrochloride tablets affects you. Bupropion hydrochloride tablets can impair your ability to perform these tasks.

What are possible side effects of bupropion hydrochloride tablets?

Bupropion hydrochloride tablets can cause serious side effects. Read this entire Medication Guide for more information about these serious side effects.

The most common side effects of bupropion hydrochloride tablets are nervousness, constipation, trouble sleeping, dry mouth, headache, nausea, vomiting, and shakiness (tremor).

If you have nausea, take your medicine with food. If you have trouble sleeping, do not take your medicine too close to bedtime.

These are not all the side effects of bupropion hydrochloride tablets. For a complete list, ask your doctor or pharmacist.

Call your doctor for medical advice about side effects. You may report side effects to FDA at 1-800-FDA-1088.

How should I store bupropion hydrochloride tablets?

- Store bupropion hydrochloride tablets at room temperature. Store out of direct sunlight. Keep bupropion hydrochloride tablets in its tightly closed bottle.

General Information about bupropion hydrochloride tablets.

- Medicines are sometimes prescribed for purposes other than those listed in a Medication Guide. Do not use bupropion hydrochloride tablets for a condition for which it was not prescribed. Do not give bupropion hydrochloride tablets to other people, even if they have the same symptoms you have. It may harm them. Keep bupropion hydrochloride tablets out of the reach of children.
- If you take a urine drug screening test, bupropion hydrochloride tablets may make the test result positive for amphetamines. If you tell the person giving you the drug screening test that you are taking bupropion hydrochloride tablets, they can do a more specific drug screening test that should not have this problem.

This Medication Guide summarizes important information about bupropion hydrochloride tablets. For more information, talk to your doctor. You can ask your doctor or pharmacist for information about bupropion hydrochloride tablets that is written for health professionals.

What are the ingredients in bupropion hydrochloride tablets?

Active ingredient: bupropion hydrochloride.

Inactive ingredients: FD&C Blue No. 2 aluminum lake, FD&C Red No. 40 aluminum lake, hydroxypropyl methylcellulose, microcrystalline cellulose, potassium chloride, pregelatinized starch, stearic acid, titanium dioxide, and triethyl citrate.

The following are registered trademarks of their respective manufacturers: KALETRA®/Abbott Laboratories; Wellbutrin SR®, Wellbutrin XL®, ZYBAN®/GlaxoSmith Kline.

This Medication Guide has been approved by the U.S. Food and Drug Administration.

04-2013M

7334

Sandoz Inc.

Princeton, NJ 08540

Repackaging Information

Please reference the How Supplied section listed above for a description of individual tablets or capsules. This drug product has been received by Aphena Pharma - TN in a manufacturer or distributor packaged configuration and repackaged in full compliance with all applicable cGMP regulations. The package configurations available from Aphena are listed below:

Count | 75mg
60 | 67544-892-53
120 | 67544-892-70
180 | 67544-892-80
360 | 67544-892-94
6000 | 67544-892-51

Count | 100mg
60 | 43353-767-53
90 | 43353-767-60
120 | 43353-767-70
180 | 43353-767-80
270 | 43353-767-92
3600 | 43353-767-83

Store between 20°-25°C (68°-77°F). See USP Controlled Room Temperature. Dispense in a tight light-resistant container as defined by USP. Keep this and all drugs out of the reach of children.

Repackaged by:
Cookeville, TN 38506
20140521SC

PRINCIPAL DISPLAY PANEL - 75mg

NDC 67544-892 - Bupropion HCI 75mg - Rx Only